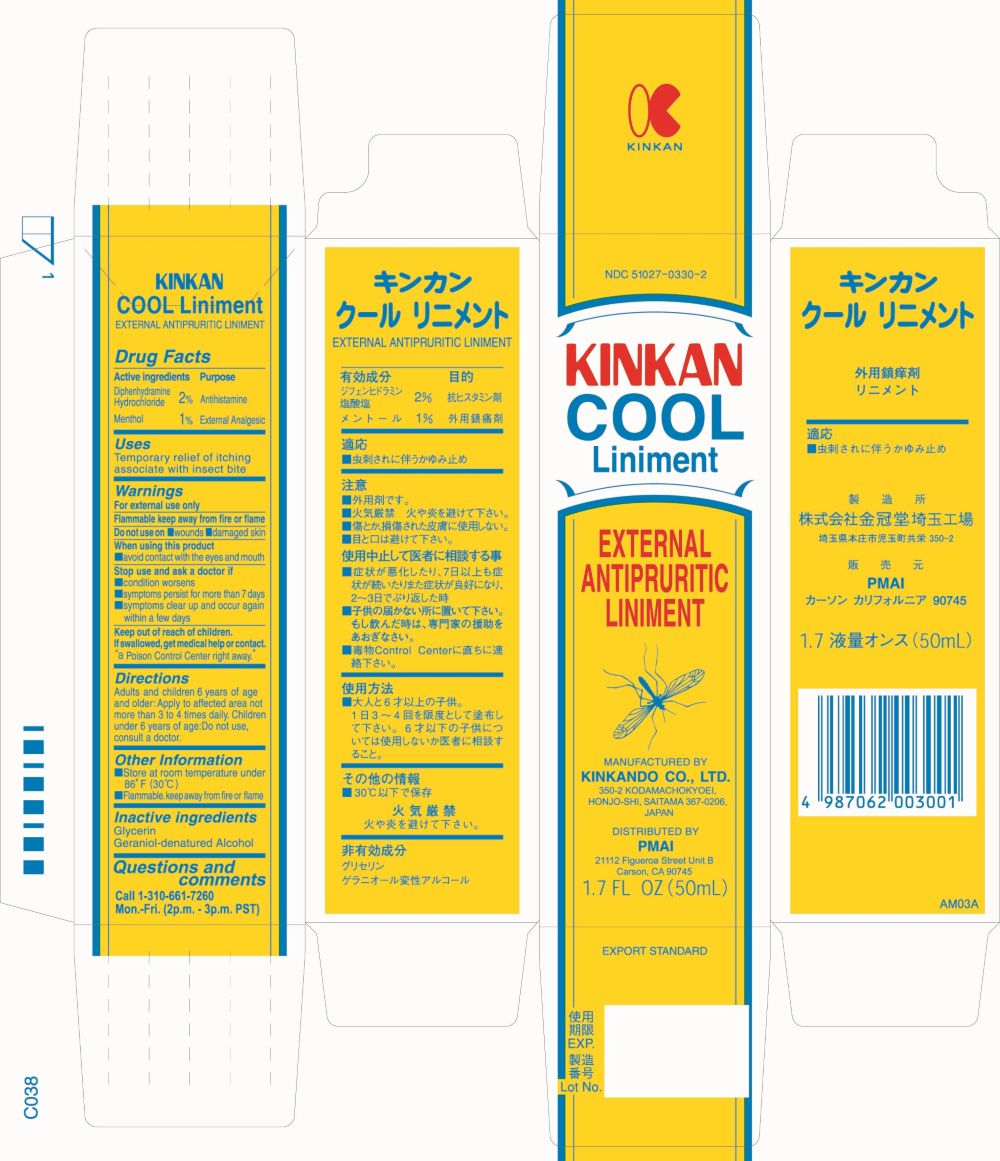 DRUG LABEL: KINKAN COOL
NDC: 51027-0330 | Form: LINIMENT
Manufacturer: KINKANDO CO., LTD .
Category: otc | Type: HUMAN OTC DRUG LABEL
Date: 20250610

ACTIVE INGREDIENTS: DIPHENHYDRAMINE HYDROCHLORIDE 1 g/50 mL; MENTHOL 0.5 g/50 mL
INACTIVE INGREDIENTS: GLYCERIN; ALCOHOL

Drug Facts

Active ingredients

Diphenhydramine Hydrochloride 2%

Menthol 1%

Purpose

Antihistamine

External Analgesic

Uses

Temporary relief of itching associate with insect bite

Warnings

For external use only

Flammable keep away from fire or flame

Do not use on

- wounds
- damaged skin

When using this product

- avoid contact with the eyes and mouth

Stop use and ask a doctor if

- condition worsens
- symptoms persist for more than 7 days
- symptoms clear up and occur again within a few days

Keep out of reach of children.

If swallowed, get medical help or contact.“a Poison Control Center right away.”

Directions

Adults and children 6 years of age and older: Apply to affected area not more than 3 to 4 times daily. Children under 6 years of age: Do not use, consult a doctor.

Other Information

- Store at room temperature under 86°F (30°C)
- Flammable. keep away from fire or flame

Inactive ingredients

Glycerin
Geraniol-denatured Alcohol

Questions and comments

Call 1-310-661-7260 Mon.-Fri. (2p.m. - 3p.m. PST)

Principal Display Panel - 50 mL Bottle Label

NDC 51027-0330-2

KINKAN
COOL
Liniment

EXTERNAL
ANTIPRURITIC
LINIMENT

MANUFACTURED BY
KINKANDO CO., LTD.350-2 KODAMACHOKYOEI,
HONJO-SHI, SAITAMA 367-0206,
JAPAN

DISTRIBUTED BY
PMAI21112 Figueroa Street Unit B

Carson, CA 90745

1.7 FL OZ (50mL)